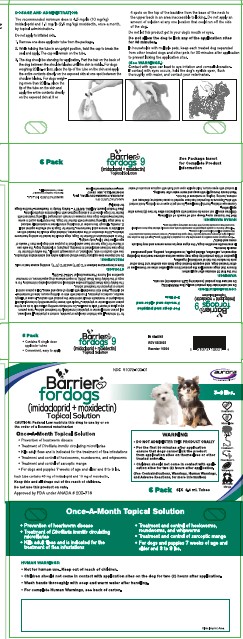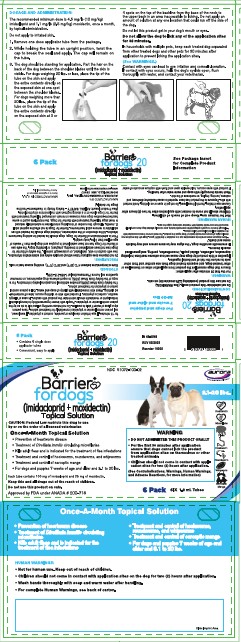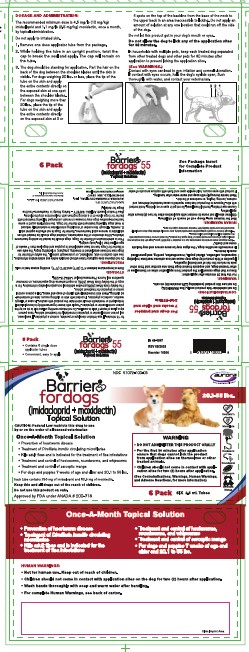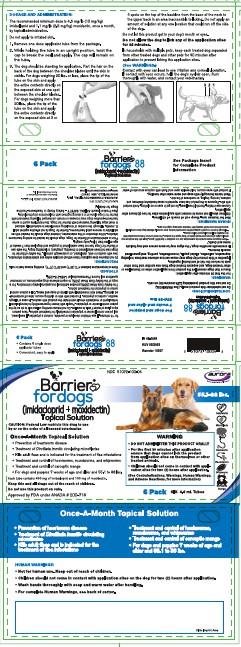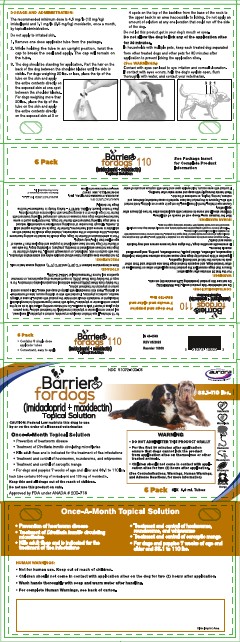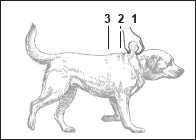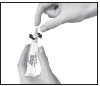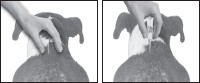 DRUG LABEL: BARRIER FOR DOGS
NDC: 51072-100 | Form: SOLUTION
Manufacturer: Aurora Pharmaceutical, Inc.
Category: animal | Type: PRESCRIPTION ANIMAL DRUG LABEL
Date: 20251211

ACTIVE INGREDIENTS: IMIDACLOPRID 100 mg/1 mL; MOXIDECTIN 25 mg/1 mL

Barrier® for Dogs
(imidacloprid+moxidectin)
Topical Solution

Once-a-month topical solution for the prevention of heartworm disease, the treatment of circulating microfilariae, kills adult fleas, is indicated for the treatment of flea infestations, the treatment and control of sarcoptic mange, as well as the treatment and control of intestinal parasite infections in dogs and puppies that are at least 7 weeks of age and that weigh at least 3 lbs.

WARNING

- DO NOT ADMINISTER THIS PRODUCT ORALLY
- For the first 30 minutes after application ensure that dogs cannot lick the product from application sites on themselves or other treated animals.
- Children should not come in contact with application sites for two (2) hours after application.

(See Contraindications, Warnings, Human Warnings, and Adverse Reactions, for more information)

CAUTION:

Federal Law restricts this drug to use by or on the order of a licensed veterinarian.

DESCRIPTION:

Barrier for Dogs (10 % imidacloprid + 2.5 % moxidectin) is a colorless to yellow ready-to-use solution packaged in single dose applicator tubes for topical treatment of dogs. The formulation and dosage schedule are designed to provide a minimum of 4.5 mg/lb (10 mg/kg) imidacloprid and 1.1 mg/lb (2.5 mg/kg) moxidectin based on body weight.

Imidacloprid is a chloronicotinyl nitroguanidine insecticide. The chemical name for imidacloprid is 1-[(6-Chloro-3-pyridinyl)methyl]-N-nitro-2-imidazolidinimine. Moxidectin is a semisynthetic macrocyclic lactone endectocide derived from the actinomycete Streptomycetes cyaneogriseus noncyanogenus. The chemical name for moxidectin is [6R, 23E, 25S(E)]-5-0- Demethyl-28-deoxy-25-(1,3-dimethyl-1-butenyl)-6,28-epoxy-23-(methoxyimino) milbemycin B.

INDICATIONS:

Barrier for Dogs is indicated for the prevention of heartworm disease caused by Dirofilaria immitis and the treatment of Dirofilaria immitis circulating microfilariae in heartworm-positive dogs. Barrier for Dogs kills adult fleas and is indicated for the treatment of flea infestations (Ctenocephalides felis). Barrier for Dogs is indicated for the treatment and control of sarcoptic mange caused by Sarcoptes scabiei var. canis. Barrier for Dogs is also indicated for the treatment and control of the following intestinal parasites:

Intestinal Parasite |  | Intestinal Stage
Intestinal Parasite |  | Adult | Immature Adult | Fourth Stage Larvae
Hookworm Species | Ancylostoma caninum | X | X | X
Hookworm Species | Uncinaria stenocephala | X | X | X
Roundworm Species | Toxocara canis | X |  | X
Roundworm Species | Toxascaris leonina | X
Whipworm | Trichuris vulpis | X

DOSAGE AND ADMINISTRATION:

The recommended minimum dose is 4.5 mg/lb (10 mg/kg) imidacloprid and 1.1 mg/lb (2.5 mg/kg) moxidectin, once a month, by topical administration.

Do not apply to irritated skin.

1. Remove one dose applicator tube from the package. As specified in the following table, administer the entire contents of the Barrier for Dogs (imidacloprid + moxidectin) tube that correctly corresponds with the body weight of the dog.
  Dog (lbs.) | Volume (mL) | Imidacloprid (mg) | Moxidectin (mg)
  3–9 | 0.4 | 40 | 10
  9.1–20 | 1.0 | 100 | 25
  20.1–55 | 2.5 | 250 | 62.5
  55.1–88 | 4.0 | 400 | 100
  88.1–110* | 5.0 | 500 | 125
  * Dogs over 110 lbs. should be treated with the appropriate combination of Barrier for Dogs tubes.
2. While holding the tube in an upright position, twist the cap to break the seal and apply. The cap will remain on the tube.

3. The dog should be standing for application. Part the hair on the back of the dog between the shoulder blades until the skin is visible. For dogs weighing 20 lbs. or less, place the tip of the tube on the skin and apply the entire contents directly on the exposed skin at one spot between the shoulder blades. For dogs weighing more than 20 lbs., place the tip of the tube on the skin and apply the entire contents directly on the exposed skin at 3 or 4 spots on the top of the backline from the base of the neck to the upper back in an area inaccessible to licking. Do not apply an amount of solution at any one location that could run off the side of the dog.

Do not let this product get in your dog's mouth or eyes. Do not allow the dog to lick any of the application sites for 30 minutes. In households with multiple pets, keep each treated dog separated from other treated dogs and other pets for 30 minutes after application to prevent licking the application sites. (See WARNINGS.)

Stiff hair, a damp appearance of the hair, pink skin, or a slight powdery residue may be observed at the application site on some animals. This is temporary and does not affect the safety and effectiveness of the product.

Shampooing 90 minutes after treatment does not reduce the effectiveness of Barrier for Dogs in the prevention of heartworm disease.

Shampooing or water immersion 4 days after treatment will not reduce the effectiveness of Barrier for Dogs in the treatment of flea infestations. However, shampooing as often as once weekly may reduce the effectiveness of the product against fleas.

Heartworm Prevention: For prevention of heartworm disease, Barrier for Dogs should be administered at one-month intervals. Barrier for Dogs may be administered year-round or at a minimum should start one month before the first expected exposure to mosquitoes and should continue at monthly intervals until one month after the last exposure to mosquitoes. If a dose is missed and a 30-day interval between doses is exceeded, administer Barrier for Dogs immediately and resume the monthly dosing schedule. When replacing another heartworm preventative product in a heartworm prevention program, the first treatment with Barrier for Dogs should be given within one month of the last dose of the former medication.

Treatment of Circulating Microfilaria: For the treatment of circulating D. immitis microfilaria in heartworm-positive dogs, Barrier for Dogs should be administered at one-month intervals. Treatment with an approved adulticide therapy is recommended because Barrier for Dogs is not effective for the treatment of adult D. immitis. (See PRECAUTIONS.)

Flea Treatment: For the treatment of flea infestations, Barrier for Dogs should be administered at one-month intervals. If the dog is already infested with fleas when the first dose of Barrier for Dogs is administered, adult fleas on the dog will be killed. However, reinfestation from the emergence of pre-existing pupae in the environment may continue to occur for six weeks or longer after treatment is initiated. Dogs treated with imidacloprid, including those with pre-existing flea allergy dermatitis have shown clinical improvement as a direct result of elimination of fleas from the dog.

Treatment and Control of Intestinal Nematode Infections:

For the treatment and control of intestinal hookworm infections caused by Ancylostoma caninum and Uncinaria stenocephala (adults, immature adults and fourth stage larvae) and roundworm infections caused by Toxocara canis (adults and fourth stage larvae), and Toxascaris leonina (adults), and whipworm infections caused by Trichuris vulpis (adults), Barrier for Dogs should be administered once as a single topical dose.

Treatment and Control of Sarcoptic Mange: For the treatment and control of sarcoptic mange caused by Sarcoptes scabiei var. canis, Barrier for Dogs should be administered as a single topical dose. A second monthly dose may be administered if necessary.

CONTRAINDICATIONS:

Do not administer this product orally. (See WARNINGS.)

Do not use this product (containing 2.5 % moxidectin) on cats.

WARNINGS

For the first 30 minutes after application:

Ensure that dogs cannot lick the product from application sites on themselves or other treated dogs, and

Separate treated dogs from one another and from other pets to reduce the risk of accidental ingestion.

Ingestion of this product by dogs may cause serious adverse reactions including depression, salivation, dilated pupils, incoordination, panting, and generalized muscle tremors.

In avermectin sensitive dogs, a the signs may be more severe and may include coma and death. b

a Some dogs are more sensitive to avermectins due to a mutation in the MDR1 gene. Dogs with this mutation may develop signs of severe avermectin toxicity if they ingest this product. The most common breeds associated with this mutation include Collies and Collie crosses.

b Although there is no specific antagonist for avermectin toxicity, even severely affected dogs have completely recovered from avermectin toxicity with intensive veterinary supportive care.

HUMAN WARNINGS:

Not for human use. Keep out of the reach of children.

Children should not come in contact with application sites for two (2) hours after application.

Causes eye irritation. Harmful if swallowed. Do not get in eyes or on clothing. Avoid contact with skin. Exposure to the product has been reported to cause headache; dizziness; and redness, burning, tingling, or numbness of the skin. Wash hands thoroughly with soap and warm water after handling.

If contact with eyes occurs, hold eyelids open and flush with copious amounts of water for 15 minutes. If eye irritation develops or persists, contact a physician. If swallowed, call poison control center or physician immediately for treatment advice. Have person sip a glass of water if able to swallow. Do not induce vomiting unless told to do so by the poison control center or physician. People with known hypersensitivity to benzyl alcohol, imidacloprid or moxidectin should administer the product with caution. In case of allergic reaction, contact a physician. If contact with skin or clothing occurs, take off contaminated clothing. Wash skin immediately with plenty of soap and water. Call a poison control center or physician for treatment advice.

The Safety Data Sheet (SDS) provides additional occupational safety information. For a copy of the Safety Data Sheet (SDS) or to report adverse drug experiences, or consumer questions call Aurora Pharmaceutical at 1-888-215-1256.

PRECAUTIONS:

Do not dispense dose applicator tubes without complete safety and administration information.

Use with caution in sick, debilitated, or underweight animals. The safety of Barrier for Dogs has not been established in breeding, pregnant, or lactating dogs. The safe use of Barrier for Dogs has not been established in puppies and dogs less than 7 weeks of age or less than 3 lbs. body weight.

Prior to administration of Barrier for Dogs, dogs should be tested for existing heartworm infection. At the discretion of the veterinarian, infected dogs should be treated with an adulticide to remove adult heartworms. The safety of Barrier for Dogs has not been evaluated when administered on the same day as an adulticide. Barrier for Dogs is not effective against adult D. immitis. Although the number of circulating microfilariae is substantially reduced in most dogs following treatment with Barrier for Dogs, the microfilaria count in some heartworm-positive dogs may increase or remain unchanged following treatment with Barrier for Dogs alone or in a dosing regimen with melarsomine dihydrochloride.

(See ADVERSE REACTIONS and ANIMAL SAFETY – Safety Study in Heartworm-Positive Dogs.)

Barrier for Dogs has not been evaluated in heartworm-positive dogs with Class 4 heartworm disease.

ADVERSE REACTIONS:

Heartworm-Negative Dogs

Field Studies: Following treatment with imidacloprid and moxidectin or an active control, dog owners reported the following post-treatment reactions:

OBSERVATION | Imidacloprid and Moxidectin Topical n = 128 | Active Control n = 68
Pruritus | 19 dogs (14.8 %) | 7 dogs (10.3 %)
Residue | 9 dogs (7.0 %) | 5 dogs (7.4 %)
Medicinal Odor | 5 dogs (3.9 %) | None observed
Lethargy | 1 dog (0.8 %) | 1 dog (1.5 %)
Inappetence | 1 dog (0.8 %) | 1 dog (1.5 %)
Hyperactivity | 1 dog (0.8 %) | None observed

During a field study using 61 dogs with pre-existing flea allergy dermatitis, one (1.6 %) dog experienced localized pruritus immediately after imidacloprid application, and one investigator noted hyperkeratosis at the application site of one dog (1.6 %).

In a field safety and effectiveness study, imidacloprid and moxidectin was administered to 92 client-owned dogs with sarcoptic mange. The dogs ranged in age from 2 months to 12.5 years and ranged in weight from 3 to 231.5 pounds. Adverse reactions in dogs treated with imidacloprid and moxidectin included hematochezia, diarrhea, vomiting, lethargy, inappetence, and pyoderma.

Laboratory Effectiveness Studies: One dog in a laboratory effectiveness study experienced weakness, depression, and unsteadiness between 6 and 9 days after application with imidacloprid and moxidectin. The signs resolved without intervention by day 10 post-application. The signs in this dog may have been related to peak serum levels of moxidectin, which vary between dogs, and occur between 1 and 21 days after application of imidacloprid and moxidectin.

The following clinical observations also occurred in laboratory effectiveness studies following application with imidacloprid and moxidectin and may be directly attributed to the drug or may be secondary to the intestinal parasite burden or other underlying conditions in the dogs: diarrhea, bloody stools, vomiting, anorexia, lethargy, coughing, ocular discharge and nasal discharge. Observations at the application sites included damp, stiff or greasy hair, the appearance of a white deposit on the hair, and mild erythema, which resolved without treatment within 2 to 48 hours.

Heartworm-Positive Dogs

Field Study: A 56-day field safety study was conducted in 214 D. immitis heartworm and microfilaria positive dogs with Class 1, 2 or 3 heartworm disease. All dogs received imidacloprid and moxidectin on Study Days 0 and 28; 108 dogs also received melarsomine dihydrochloride on Study Days – 14, 14, and 15. All dogs were hospitalized for a minimum of 12 hours following each treatment. Effectiveness against circulating D. immitis microfilariae was > 90 % at five of six sites; however, one site had an effectiveness of 73.3 %. The microfilaria count in some heartworm-positive dogs increased or remained unchanged following treatment with imidacloprid and moxidectin alone or in a dosing regimen with melarsomine dihydrochloride.

Following treatment with imidacloprid and moxidectin alone or in a dosing regimen with melarsomine dihydrochloride, the following adverse reactions were observed:

Adverse Reaction | Dogs Treated with Imidacloprid and Moxidectin Only n = 106 | Dogs Treated with Imidacloprid and Moxidectin + Melarsomine n = 108
Cough | 24 (22.6 %) | 25 (23.1 %)
Lethargy | 14 (13.2 %) | 42 (38.9 %)
Vomiting | 11 (10.4 %) | 18 (16.7 %)
Diarrhea, including hemorrhagic | 10 (9.4 %) | 22 (20.4 %)
Inappetence | 7 (6.6 %) | 19 (17.6 %)
Dyspnea | 6 (5.7 %) | 10 (9.3 %)
Tachypnea | 1 (< 1 %) | 7 (6.5 %)
Pulmonary Hemorrhage | 0 | 1 (< 1 %)
Death | 0 | 3 (2.8 %)

Three dogs treated with imidacloprid and moxidectin in a dosing regimen with melarsomine dihydrochloride died of pulmonary embolism from dead and dying heartworms. One dog, treated with imidacloprid and moxidectin and melarsomine dihydrochloride, experienced pulmonary hemorrhage and responded to supportive medical treatment. Following the first treatment with imidacloprid and moxidectin alone, two dogs experienced adverse reactions (coughing, vomiting, and dyspnea) that required hospitalization. In both groups, there were more adverse reactions to imidacloprid and moxidectin following the first treatment than the second treatment.

To report a suspected adverse reaction, call Aurora Pharmaceutical at 1-888-215-1256.

Post-Approval Experience

The following adverse events are based on post-approval adverse drug experience reporting. Not all adverse reactions are reported to FDA CVM. It is not always possible to reliably estimate the adverse event frequency or establish a causal relationship to product exposure using this data. The following adverse events reported in dogs are listed in decreasing order of reporting frequency: depression/lethargy, vomiting, pruritus, diarrhea, anorexia, hyperactivity, ataxia, trembling, hypersalivation, application site reactions (alopecia, pruritus, lesions, and erythema), seizures, and anaphylaxis/anaphylactic reactions (hives, urticaria, facial swelling, edema of the head).

Serious reactions, including neurologic signs and death have been reported when cats have been exposed (orally and topically) to this product.

In humans, nausea, numbness or tingling of the mouth/lips and throat, ocular and dermal irritation, pruritus, headache, vomiting, diarrhea, depression and dyspnea have been reported following exposure to this product.

Contact Information:

To report suspected adverse drug experiences and/or obtain a copy of the SDS or for technical assistance, contact Aurora Pharmaceutical at 1-888-215-1256 or www.aurorapharmaceutical.com.

For additional information about adverse drug experience reporting for animal drugs, contact FDA at 1-888-FDA-VETS or online at http://www.fda.gov/reportamimalae.

ANIMAL SAFETY:

Heartworm-Negative Dogs

Field Study: In a controlled, double-masked, field safety study, imidacloprid and moxidectin was administered to 128 dogs of various breeds, 3 months to 15 years of age, weighing 4 to 157 pounds. Imidacloprid and moxidectin was used safely in dogs concomitantly receiving ACE inhibitors, anticonvulsants, antihistamines, antimicrobials, chondroprotectants, corticosteroids, immunotherapeutics, MAO inhibitors, NSAIDs, ophthalmic medications, sympathomimetics, synthetic estrogens, thyroid hormones, and urinary acidifiers. Owners reported the following signs in their dogs after application of imidacloprid and moxidectin: pruritus, flaky/ greasy residue at the treatment site, medicinal odor, lethargy, inappetence, and hyperactivity.

(See ADVERSE REACTIONS.)

Safety Study in Puppies: Imidacloprid and moxidectin was applied topically at 1, 3 and 5X the recommended dose to 7-week-old Beagle puppies once every 2 weeks for 6 treatments on days 0, 14, 28, 42, 56, and 70. Loose stools and diarrhea were observed in all groups, including the controls, throughout the study. Vomiting was seen in one puppy from the 1X treatment group (day 57), in two puppies from the 3X treatment group (days 1 and 79), and in one puppy from the 5X treatment group (day 1). Two puppies each in the 1X, 3X, and 5X groups had decreased appetites within 24 hours post-dosing. One puppy in the 1X treatment group had pruritus for one hour following the fifth treatment. A puppy from the 5X treatment group displayed rapid, difficult breathing from 4 to 8 hours following the second treatment.

Dermal Dose Tolerance Study: Imidacloprid and moxidectin was administered topically to 8-month-old Beagle dogs at 10X the recommended dose once. One dog showed signs of treatment site irritation after application. Two dogs vomited, one at 6 hours and one at 6 days post-treatment. Increased RBC, hemoglobin, activated partial thromboplastin, and direct bilirubin were observed in the treated group. Dogs in the treated group did not gain as much weight as the control group.

Oral Safety Study in Beagles: Imidacloprid and moxidectin was administered once orally at the recommended topical dose to 12 dogs. Six dogs vomited within 1 hour of receiving the test article, 2 of these dogs vomited again at 2 hours, and 1 dog vomited again up to 18 hours post-dosing. One dog exhibited shaking (nervousness) 1 hour post-dosing. Another dog exhibited abnormal neurological signs (circling, ataxia, generalized muscle tremors, and dilated pupils with a slow pupillary light response) starting at 4 hours post-dosing through 18 hours postdosing. Without treatment, this dog was neurologically normal at 24 hours and had a normal appetite by 48 hours post-dosing. (See CONTRAINDICATIONS.)

Dermal Safety Study in Ivermectin-Sensitive Collies:

Imidacloprid and moxidectin was administered topically at 3 and 5X the recommended dose every 28 days for 3 treatments to Collies which had been prescreened for avermectin sensitivity. No clinical abnormalities were observed.

Oral Safety Study in Ivermectin-Sensitive Collies:

Imidacloprid and moxidectin was administered orally to 5 pre-screened ivermectinsensitive Collies. The Collies were asymptomatic after ingesting 10 % of the minimum labeled dose. At 40 % of the minimum recommended topical dose, 4 of the dogs experienced neurological signs indicative of avermectin toxicity including depression, ataxia, mydriasis, salivation, muscle fasciculation, and coma, and were euthanized.

(See CONTRAINDICATIONS.)

Heartworm-Positive Dogs

Laboratory Safety Study in Heartworm-Positive Dogs: Imidacloprid and moxidectin was administered topically at 1 and 5X the recommended dose every 14 days for 3 treatments to dogs with adult heartworm infections and circulating microfilaria. At 5X, one dog was observed vomiting three hours after the second treatment. Hypersensitivity reactions were not seen in the 5X treatment group. Microfilaria counts decreased with treatment.

STORAGE INFORMATION:

Store at temperatures between 4°C (39°F) and 25°C (77°F), avoiding excess heat or cold.

HOW SUPPLIED:

Applications Per Package

6 x 0.4 mL tubes

6 x 1.0 mL tubes

6 x 2.5 mL tubes

6 x 4.0 mL tubes

6 x 5.0 mL tubes

55-1554 06/2025

Approved by FDA under ANADA # 200-718

MANUFACTURED BY:
AURORA PHARMACEUTICAL, INC.
NORTHFIELD, MN 55057
www.aurorapharmaceutical.com

MANUFACTURED IN U.S.A.

Barrier is a registered trademark of Aurora Pharmaceutical, Inc.

Principal Display Panel - 0.4 mL Carton Label

3 – 9 lbs

Heartworm

Microfilaria

Fleas

Hookworm

Roundworm

Whipworm

Sarcoptic
Mange

6 Pack

Barrier® for dogs
(imidacloprid+moxidectin)
Topical Solution

CAUTION: Federal Law restricts this drug to use by or on the order of a licensed veterinarian

Once-A-Month Topical Solution

Prevention of heartworm disease
Treatment of Dirofilaria immitis circulating microfilariae
Kills adult fleas and is indicated for the treatment of flea infestations
Treatment and control of hookworms, roundworms, and whipworms
Treatment and control of sarcoptic mange
For dogs and puppies 7 weeks of age and older and 3 to 9 lbs.
WARNING

DO NOT ADMINISTER THIS PRODUCT ORALLY
For the first 30 minutes after application ensure that dogs cannot lick the product from application sites on themselves or other treated animals.
Children should not come in contact with application sites for two (2) hours after application.
(See Contraindications, Warnings, Human Warnings, and Adverse Reactions, for more information)

Each tube contains 40 mg of imidacloprid and 10 mg of moxidectin.

Keep this and all drugs out of the reach of children.

Do not use this product on cats.

Approved by FDA under ANADA # 200-718

SIX 0.4 mL Tubes

NDC 51072-100-01

IN 40-1545 05/2025

Principal Display Panel - 1.0 mL Carton Label

9.1 - 20 lbs.

Heartworm

Microfilaria

Fleas

Hookworm

Roundworm

Whipworm

Sarcoptic
Mange

6 Pack

Barrier® for dogs
(imidacloprid+moxidectin)
Topical Solution

CAUTION: Federal Law restricts this drug to use by or on the order of a licensed veterinarian

Once-A-Month Topical Solution

Prevention of heartworm disease
Treatment of Dirofilaria immitis circulating microfilariae
Kills adult fleas and is indicated for the treatment of flea infestations
Treatment and control of hookworms, roundworms, and whipworms
Treatment and control of sarcoptic mange
For dogs and puppies 7 weeks of age and older and 9.1 to 20 lbs.
WARNING

DO NOT ADMINISTER THIS PRODUCT ORALLY
For the first 30 minutes after application ensure that dogs cannot lick the product from application sites on themselves or other treated animals.
Children should not come in contact with application sites for two (2) hours after application.
(See Contraindications, Warnings, Human Warnings, and Adverse Reactions, for more information)

Each tube contains 100 mg of imidacloprid and 25 mg of moxidectin.

Keep this and all drugs out of the reach of children.

Do not use this product on cats.

Approved by FDA under ANADA # 200-718

SIX 1.0 mL Tubes

NDC 51072-100-02

IN 40-1546 05/2025

Principal Display Panel - 2.5 mL Carton Label

20.1 – 55 lbs

Heartworm

Microfilaria

Fleas

Hookworm

Roundworm

Whipworm

Sarcoptic
Mange

6 Pack

Barrier® for dogs
(imidacloprid+moxidectin)
Topical Solution

CAUTION: Federal Law restricts this drug to use by or on the order of a licensed veterinarian

Once-A-Month Topical Solution

Prevention of heartworm disease
Treatment of Dirofilaria immitis circulating microfilariae
Kills adult fleas and is indicated for the treatment of flea infestations
Treatment and control of hookworms, roundworms, and whipworms
Treatment and control of sarcoptic mange
For dogs and puppies 7 weeks of age and older and 20.1 to 55 lbs.
WARNING

DO NOT ADMINISTER THIS PRODUCT ORALLY
For the first 30 minutes after application ensure that dogs cannot lick the product from application sites on themselves or other treated animals.
Children should not come in contact with application sites for two (2) hours after application.
(See Contraindications, Warnings, Human Warnings, and Adverse Reactions, for more information)

Each tube contains 250 mg of imidacloprid and 62.5 mg of moxidectin.

Keep this and all drugs out of the reach of children.

Do not use this product on cats.

Approved by FDA under ANADA # 200-718

SIX 2.5 mL Tubes

NDC 51072-100-03

IN 40-1547 05/2025

Principal Display Panel - 4.0 mL Carton Label

55.1 – 88 lbs

Heartworm

Microfilaria

Fleas

Hookworm

Roundworm

Whipworm

Sarcoptic
Mange

6 Pack

Barrier® for dogs
(imidacloprid+moxidectin)
Topical Solution

CAUTION: Federal Law restricts this drug to use by or on the order of a licensed veterinarian

Once-A-Month Topical Solution

- Prevention of heartworm disease
- Treatment of Dirofilaria immitis circulating microfilariae
- Kills adult fleas and is indicated for the treatment of flea infestations
- Treatment and control of hookworms, roundworms, and whipworms
- Treatment and control of sarcoptic mange
- For dogs and puppies 7 weeks of age and older and 55.1 to 88 lbs.

WARNING

- DO NOT ADMINISTER THIS PRODUCT ORALLY
- For the first 30 minutes after application ensure that dogs cannot lick the product from application sites on themselves or other treated animals.
- Children should not come in contact with application sites for two (2) hours after application.

(See Contraindications, Warnings, Human Warnings, and Adverse Reactions, for more information)

Each tube contains 400 mg of imidacloprid and 100 mg of moxidectin.

Keep this and all drugs out of the reach of children.

Do not use this product on cats.

Approved by FDA under ANADA # 200-718

SIX 4.0 mL Tubes

NDC 51072-100-04

IN 40-1548 05/2025

Principal Display Panel - 5.0 mL Carton Label

88.1 – 110 lbs

Heartworm

Microfilaria

Fleas

Hookworm

Roundworm

Whipworm

Sarcoptic
Mange

6 Pack

Barrier® for dogs
(imidacloprid+moxidectin)
Topical Solution

CAUTION: Federal Law restricts this drug to use by or on the order of a licensed veterinarian

Once-A-Month Topical Solution

Prevention of heartworm disease
Treatment of Dirofilaria immitis circulating microfilariae
Kills adult fleas and is indicated for the treatment of flea infestations
Treatment and control of hookworms, roundworms, and whipworms
Treatment and control of sarcoptic mange
For dogs and puppies 7 weeks of age and older and 88.1 to 110 lbs.
WARNING

DO NOT ADMINISTER THIS PRODUCT ORALLY
For the first 30 minutes after application ensure that dogs cannot lick the product from application sites on themselves or other treated animals.
Children should not come in contact with application sites for two (2) hours after application.
(See Contraindications, Warnings, Human Warnings, and Adverse Reactions, for more information)

Each tube contains 500 mg of imidacloprid and 125 mg of moxidectin.

Keep this and all drugs out of the reach of children.

Do not use this product on cats.

Approved by FDA under ANADA # 200-718

SIX 5.0 mL Tubes

NDC 51072-100-05

IN 40-1549 05/2025